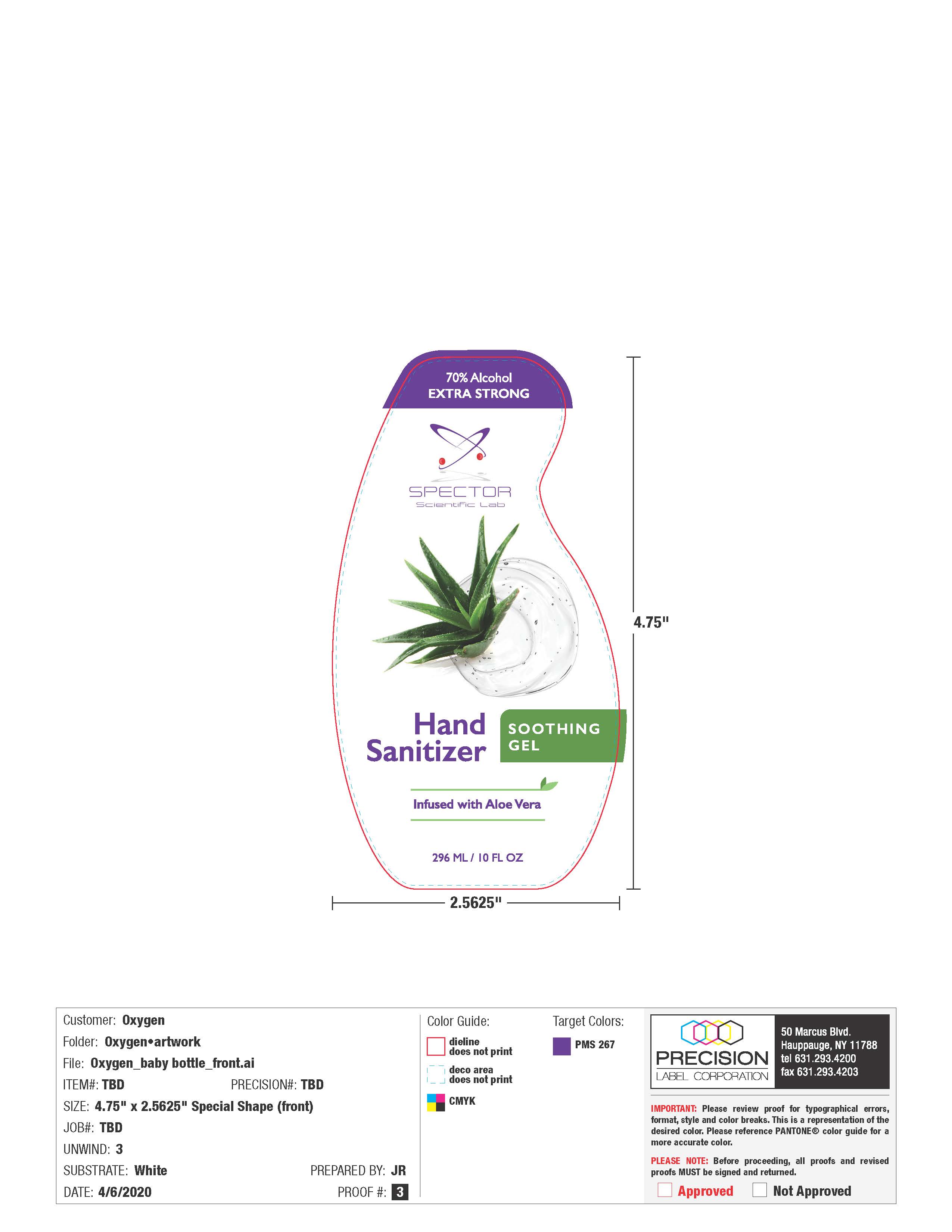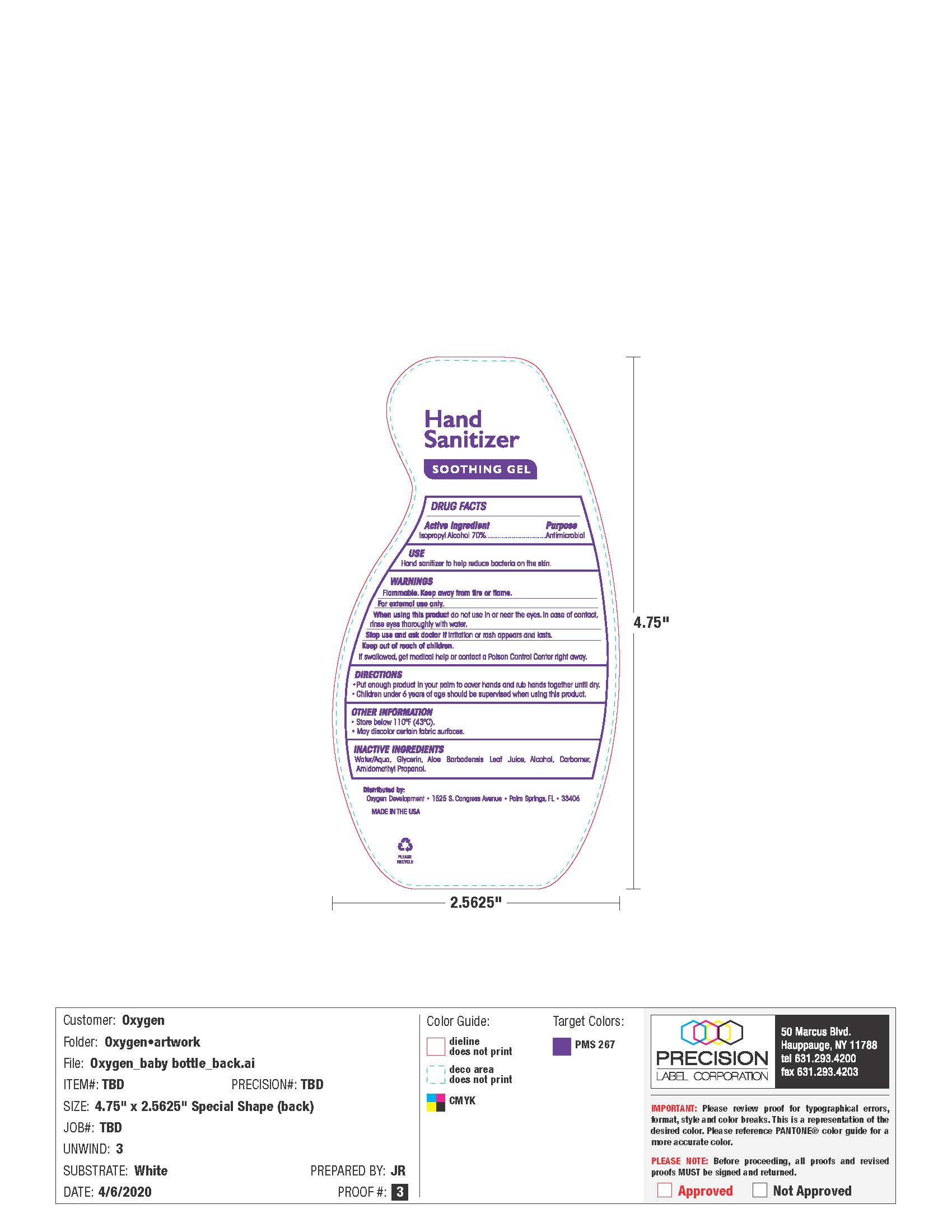 DRUG LABEL: Hand Sanitizer
NDC: 61354-046 | Form: GEL
Manufacturer: Oxygen Development LLC
Category: otc | Type: HUMAN OTC DRUG LABEL
Date: 20220111

ACTIVE INGREDIENTS: ISOPROPYL ALCOHOL 70.92 mL/100 mL
INACTIVE INGREDIENTS: GLYCERIN 1.49 mL/100 mL; CARBOMER HOMOPOLYMER, UNSPECIFIED TYPE 0.5 mL/100 mL; WATER

70% Alcohol Extra Strong Spector Scientific Lab hand Sanitizer Infused with Aloe Vera

Active Ingredient(s)

Isopropyl Alcohol 70%

Purpose

Antimicrobial

Use

Hand Sanitizer to help reduce bacteria on the skin.

Warnings

Flammable. Keep away from heat or flame. For external use only.

when using

When using this do not use in or near the eyes. In case of contact with eyes, rinse eyes thoroughly with water.
Stop use and ask a doctor if irritation or rash appears and lasts.
Keep out of reach of children. If swallowed, get medical help or contact a Poison Control Center right away.

Stop use

Stop use and ask a doctor if irritation or rash appears and lasts.

Keep out of reach of children. If swallowed, get medical help or contact a Poison Control Center right away.

Directions

- Put enough product in your palm to cover hands and rub hands together until dry.
- Children under 6 years of age should be supervised when usign this product.

Other information

- Store below 110F (43C)
- May discolor certain fabric surfaces

Inactive ingredients

Water / aqua, Glycerin, Aloe Barbadensis Leaf juice, Alcohol, Carbomer, Amidomethyl Propanol